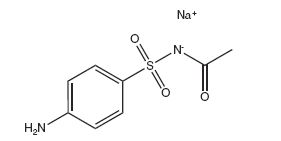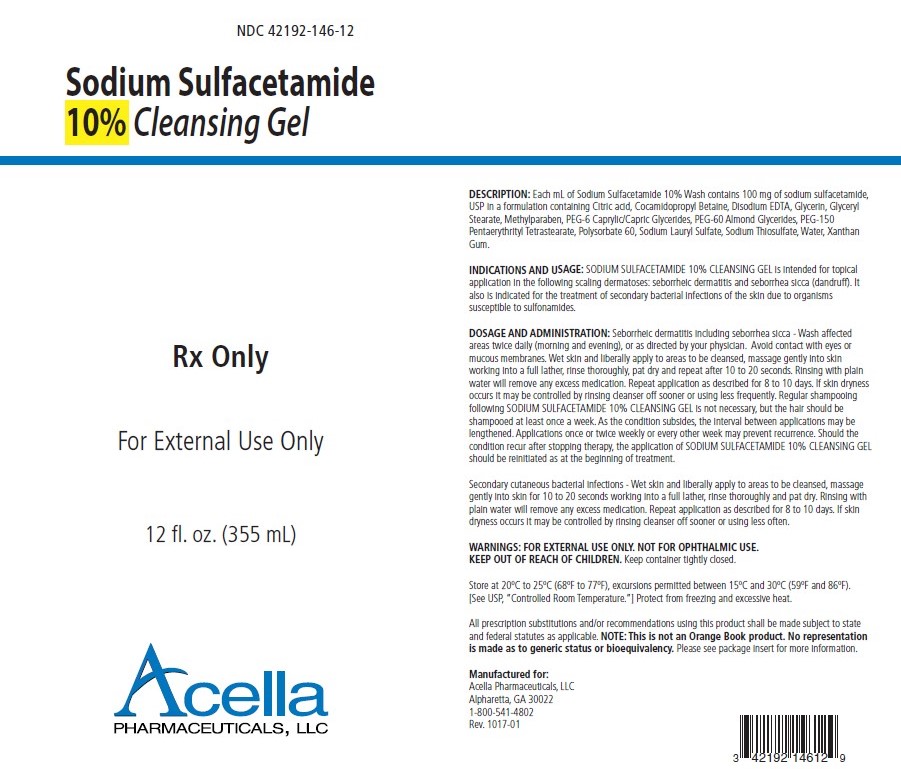 DRUG LABEL: Sodium Sulfacetamide
NDC: 42192-146 | Form: GEL
Manufacturer: Acella Pharmaceuticals, LLC
Category: prescription | Type: HUMAN PRESCRIPTION DRUG LABEL
Date: 20250909

ACTIVE INGREDIENTS: SULFACETAMIDE SODIUM 100 mg/1 mL
INACTIVE INGREDIENTS: CITRIC ACID MONOHYDRATE; COCAMIDOPROPYL BETAINE; EDETATE DISODIUM; GLYCERIN; GLYCERYL MONOSTEARATE; METHYLPARABEN; MEDIUM-CHAIN TRIGLYCERIDES; PENTAERYTHRITYL TETRASTEARATE; POLYSORBATE 60; SODIUM LAURYL SULFATE; SODIUM THIOSULFATE; WATER; XANTHAN GUM; PEG-60 ALMOND GLYCERIDES; PEG-6 CAPRYLIC/CAPRIC GLYCERIDES; PEG-150 PENTAERYTHRITYL TETRASTEARATE

SODIUM SULFACETAMIDE 10% CLEANSING GEL

Rx Only

FOR EXTERNAL USE ONLY. NOT FOR OPHTHALMIC USE.

DESCRIPTION

DESCRIPTION:Each mL of SODIUM SULFACETAMIDE 10% CLEANSING GEL contains 100 mg of sodium sulfacetamide, USP in a formulation containing Citric acid, Cocamidopropyl Betaine, Disodium EDTA, Glycerin, Glyceryl Stearate, Methylparaben, PEG-6 Caprylic/Capric Glycerides, PEG-60 Almond Glycerides, PEG-150 Pentaerythrityl Tetrastearate, Polysorbate 60, Sodium Lauryl Sulfate, Sodium Thiosulfate, Water, Xanthan Gum.

Sodium sulfacetamide is C8H9N2NaO3S·H2O with molecular weight of 254.24. Chemically, it is N-[(4-aminophenyl)sulfonyl]-acetamide, monosodium salt, monohydrate. The structural formula is:

Sodium sulfacetamide is an odorless, white, crystalline powder with a bitter taste. It is freely soluble in water, sparingly soluble in alcohol, while practically insoluble in benzene, in chloroform and in ether.

CLINICAL PHARMACOLOGY

CLINICAL PHARMACOLOGY:Sodium sulfacetamide exerts a bacteriostatic effect against sulfonamide sensitive Gram-positive and Gram-negative microorganisms commonly isolated from secondary cutaneous pyogenic infections. It acts by restricting the synthesis of folic acid required by bacteria for growth, by its competition with para-aminobenzoic acid. There is no clinical data available on the degree and rate of systemic absorption of SODIUM SULFACETAMIDE 10% CLEANSING GEL when applied to the skin or scalp. However, significant absorption of sodium sulfacetamide through the skin has been reported. The following in vitro data is available but the clinical significance is unknown. Organisms that show susceptibility to sodium sulfacetamide are: Streptococci, Staphylococci, E. coli, Klebsiella pneumoniae, Pseudomonas pyocyanea, Salmonella species, Proteus vulgaris, Nocardia and Actinomyces.

INDICATIONS AND USAGE:SODIUM SULFACETAMIDE 10% CLEANSING GEL is intended for topical application in the following scaling dermatoses: seborrheic dermatitis and seborrhea sicca (dandruff). It also is indicated for the treatment of secondary bacterial infections of the skin due to organisms susceptible to sulfonamides.

CONTRAINDICATIONS

CONTRAINDICATIONS:SODIUM SULFACETAMIDE 10% CLEANSING GEL is contraindicated in persons with known or suspected hypersensitivity to sulfonamides or to any of the ingredients of the product.

WARNINGS

WARNINGS:Sulfonamides are known to cause Stevens-Johnson syndrome in hypersensitive individuals. Stevens-Johnson syndrome also has been reported following the use of sodium sulfacetamide topically. Cases of drug-induced systemic lupus erythematosus from topical sulfacetamide also have been reported. In one of these cases, there was a fatal outcome. KEEP OUT OF THE REACH OF CHILDREN.

PRECAUTIONS:

FOR EXTERNAL USE ONLY. NOT FOR OPHTHALMIC USE.

General: Nonsusceptible organisms, including fungi, may proliferate with the use of this preparation. Hypersensitivity reactions may recur when a sulfonamide is readministered, irrespective of the route of administration, and cross hypersensitivity between different sulfonamides may occur. If SODIUM SULFACETAMIDE 10% CLEANSING GEL produces signs of hypersensitivity or other untoward reactions, discontinue use of the preparation. Systemic absorption of topical sulfonamides is greater following application to large, infected, abraded, denuded or severely burned areas. Under these circumstances, any of the adverse effects produced by the systemic administration of these agents could potentially occur, and appropriate observations and laboratory determinations should be performed.

PATIENT COUNSELING INFORMATION

Information for Patients: Patients should discontinue SODIUM SULFACETAMIDE 10% CLEANSING GEL if the condition becomes worse, or if a rash develops in the area being treated or elsewhere. SODIUM SULFACETAMIDE 10% CLEANSING GEL also should be discontinued promptly and the physician notified if any arthritis, fever or sores in the mouth develop.

DRUG INTERACTIONS

Drug Interactions: SODIUM SULFACETAMIDE 10% CLEANSING GEL is incompatible with silver preparations.

Pharmacology: SODIUM SULFACETAMIDE 10% CLEANSING GEL has a bacteriostatic effect against Gram-positive and Gram-negative microorganisms commonly isolated from secondary cutaneous pyogenic infections.

CARCINOGENESIS AND MUTAGENESIS AND IMPAIRMENT OF FERTILITY

Carcinogenesis, Mutagenesis and Impairment of Fertility: Long-term animal studies for carcinogenic potential have not been performed on SODIUM SULFACETAMIDE 10% CLEANSING GEL to date. Studies on reproduction and fertility also have not been performed. Chromosomal nondisjunction has been reported in the yeast, Saccharomyces cerevisiae, following application of sodium sulfacetamide. The significance of this finding to the topical use of sodium sulfacetamide in the human is unknown.

PREGNANCY

Pregnancy: Category C. Animal reproduction studies have not been conducted with SODIUM SULFACETAMIDE 10% CLEANSING GEL. It is also not known whether SODIUM SULFACETAMIDE 10% CLEANSING GEL can affect reproduction capacity or cause fetal harm when administered to a pregnant woman. SODIUM SULFACETAMIDE 10% CLEANSING GEL should be used by a pregnant woman only if clearly needed or when potential benefits outweigh potential hazards to the fetus.

NURSING MOTHERS

Nursing Mothers: It is not known whether this drug is excreted in human milk. Because many drugs are excreted in human milk, caution should be exercised when SODIUM SULFACETAMIDE 10% CLEANSING GEL is administered to a nursing woman.

PEDIATRIC USE

Pediatric Use: Safety and effectiveness in children under the age of 12 years has not been established.

ADVERSE REACTIONS

ADVERSE REACTIONS:Reports of irritation and hypersensitivity to sodium sulfacetamide are uncommon. The following adverse reactions, reported after administration of sterile ophthalmic sodium sulfacetamide, are noteworthy: instances of Stevens-Johnson syndrome and instances of local hypersensitivity which progressed to a syndrome resembling systemic lupus erythematosus; in one case a fatal outcome was reported (see WARNINGS). Call your doctor for medical advice about side effects.

OVERDOSAGE

OVERDOSAGE:The oral LD50 of sulfacetamide in mice is 16.5 g/kg. In the event of overdosage, emergency treatment should be started immediately.

To report SUSPECTED ADVERSE REACTIONS, contact the FDA at 1-800-FDA-1088 or www.fda.gov/medwatch.

Manifestations: Overdosage may cause nausea and vomiting. Large oral overdosage may cause hematuria, crystalluria and renal shutdown due to the precipitation of sulfa crystals in the renal tubules and the urinary tract. For treatment, contact your local Poison Control Center or your doctor.

DOSAGE AND ADMINISTRATION:Seborrheic dermatitis including seborrhea sicca - Wash affected areas twice daily (morning and evening), or as directed by your physician. Avoid contact with eyes or mucous membranes. Wet skin and liberally apply to areas to be cleansed, massage gently into skin working into a full lather, rinse thoroughly, pat dry and repeat after 10 to 20 seconds. Rinsing with plain water will remove any excess medication. Repeat application as described for 8 to 10 days. lf skin dryness occurs it may be controlled by rinsing cleanser off sooner or using less frequently. Regular shampooing following SODIUM SULFACETAMIDE 10% CLEANSING GEL is not necessary, but the hair should be shampooed at least once a week. As the condition subsides, the interval between applications may be lengthened. Applications once or twice weekly or every other week may prevent recurrence. Should the condition recur after stopping therapy, the application of SODIUM SULFACETAMIDE 10% CLEANSING GEL should be reinitiated as at the beginning of treatment.

Secondary cutaneous bacterial infections - Wet skin and liberally apply to areas to be cleansed, massage gently into skin for 10 to 20 seconds working into a full lather, rinse thoroughly and pat dry. Rinsing with plain water will remove any excess medication. Repeat application as described for 8 to 10 days. If skin dryness occurs it may be controlled by rinsing cleanser off sooner or using less often.

HOW SUPPLIED:

SODIUM SULFACETAMIDE 10% CLEANSING GEL is available in a 12 fl. oz. (355 mL) bottle, NDC 42192-146-12.

STORAGE AND HANDLING

Store at 20ºC to 25ºC (68ºF to 77ºF), excursions permitted between 15ºC and 30ºC (59ºF and 86ºF). [See USP, “Controlled Room Temperature.”] Protect from freezing and excessive heat.

Note: Protect from freezing and excessive heat. The product may tend to darken slightly on storage. Slight discoloration does not impair the efficacy or safety of the product. Keep container or packet tightly closed.

A slight yellowish discoloration may occur on occasion when an excessive amount of the product is used and comes in contact with white fabrics. This discoloration is easily removed by normal laundering; bleaching is not necessary.

All prescription substitutions and/or recommendations using this product shall be made subject to state and federal statutes as applicable. Please NOTE: This is not an Orange Book product and has not been subjected to FDA therapeutic or other equivalency testing. No representation is made as to generic status or bioequivalency.Each person recommending a prescription substitution using this product shall make such recommendation based on his/her professional knowledge and opinion, upon evaluating the active ingredients, inactive ingredients, excipients and chemical information provided herein.

Manufactured for:
Acella Pharmaceuticals, LLC
11675 Great Oaks Way
Alpharetta, GA 30022
1-800-541-4802

Rev. 0914

PACKAGE LABEL - 12 fl. oz. (355 mL) bottle

NDC 42192-146-12

Sodium Sulfacetamide
10% Cleansing Gel

Rx Only

For External Use Only

12 fl. oz. (355 mL)

Acella
PHARMACEUTICALS, LLC